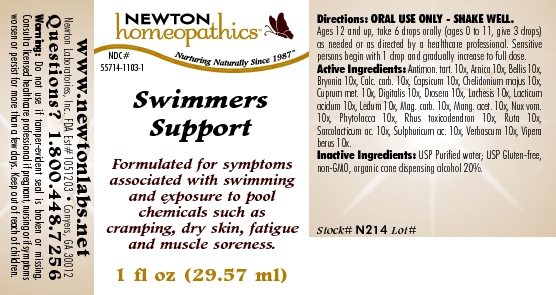 DRUG LABEL: Swimmers Support 
NDC: 55714-1103 | Form: LIQUID
Manufacturer: Newton Laboratories, Inc.
Category: homeopathic | Type: HUMAN OTC DRUG LABEL
Date: 20110301

ACTIVE INGREDIENTS: Antimony Potassium Tartrate 10 [hp_X]/1 mL; Arnica Montana 10 [hp_X]/1 mL; Bellis Perennis 10 [hp_X]/1 mL; Bryonia Alba Root 10 [hp_X]/1 mL; Oyster Shell Calcium Carbonate, Crude 10 [hp_X]/1 mL; Capsicum 10 [hp_X]/1 mL; Chelidonium Majus 10 [hp_X]/1 mL; Copper 10 [hp_X]/1 mL; Digitalis 10 [hp_X]/1 mL; Drosera Rotundifolia Flowering Top 10 [hp_X]/1 mL; Lachesis Muta Venom 10 [hp_X]/1 mL; Lactic Acid, Dl- 10 [hp_X]/1 mL; Ledum Palustre Twig 10 [hp_X]/1 mL; Magnesium Carbonate 10 [hp_X]/1 mL; Manganese Acetate Tetrahydrate 10 [hp_X]/1 mL; Strychnos Nux-vomica Seed 10 [hp_X]/1 mL; Phytolacca Americana Root 10 [hp_X]/1 mL; Toxicodendron Pubescens Leaf 10 [hp_X]/1 mL; Ruta Graveolens Flowering Top 10 [hp_X]/1 mL; Lactic Acid, L- 10 [hp_X]/1 mL; Sulfuric Acid 10 [hp_X]/1 mL; Verbascum Thapsus 10 [hp_X]/1 mL; Vipera Berus Venom 10 [hp_X]/1 mL
INACTIVE INGREDIENTS: Alcohol

Swimmers Support

INDICATIONS & USAGE SECTION

Swimmers Support Formulated for symptoms associated with swimming and exposure to pool chemicals such as cramping, dry skin, fatigue and muscle soreness.

DOSAGE & ADMINISTRATION SECTION

Directions: ORAL USE ONLY - SHAKE WELL. Ages 12 and up, take 6 drops orally (ages 0 to 11, give 3 drops) as needed or as directed by a healthcare professional. Sensitive persons begin with 1 drop and gradually increase to full dose .

OTC - ACTIVE INGREDIENT SECTION

Antimon. tart. 10x, Arnica 10x, Bellis 10x, Bryonia 10x, Calc. carb. 10x, Capsicum 10x, Chelidonium majus 10x, Cuprum met. 10x, Digitalis 10x, Drosera 10x, Lachesis 10x, Lacticum acidum 10x, Ledum 10x, Mag. carb. 10x, Mang. acet. 10x, Nux vom.10x, Phytolacca 10x, Rhus toxicodendron 10x, Ruta 10x, Sarcolacticum ac. 10x, Sulphuricum ac. 10x, Verbascum 10x, Vipera berus 10x.

OTC - PURPOSE SECTION

Formulated for symptoms associated with swimming and exposure to pool chemicals such as cramping, dry skin, fatigue and muscle soreness.

INACTIVE INGREDIENT SECTION

Inactive Ingredients: USP Purified Water; USP Gluten-free, non-GMO, organic cane dispensing alcohol 20%.

QUESTIONS SECTION

www.newtonlabs.net Newton Laboratories, Inc. FDA Est # 1051203 - Conyers, GA 30012
Questions? 1.800.448.7256

WARNINGS SECTION

Warning: Do not use if tamper - evident seal is broken or missing. Consult a licensed healthcare professional if pregnant, nursing or if symptoms worsen or persist for more than a few days. Keep out of reach of children.

OTC - PREGNANCY OR BREAST FEEDING SECTION

Consult a licensed healthcare professional if pregnant, nursing or if symptoms worsen or persist for more than a few days.

OTC - KEEP OUT OF REACH OF CHILDREN SECTION

Keep out of reach of children.